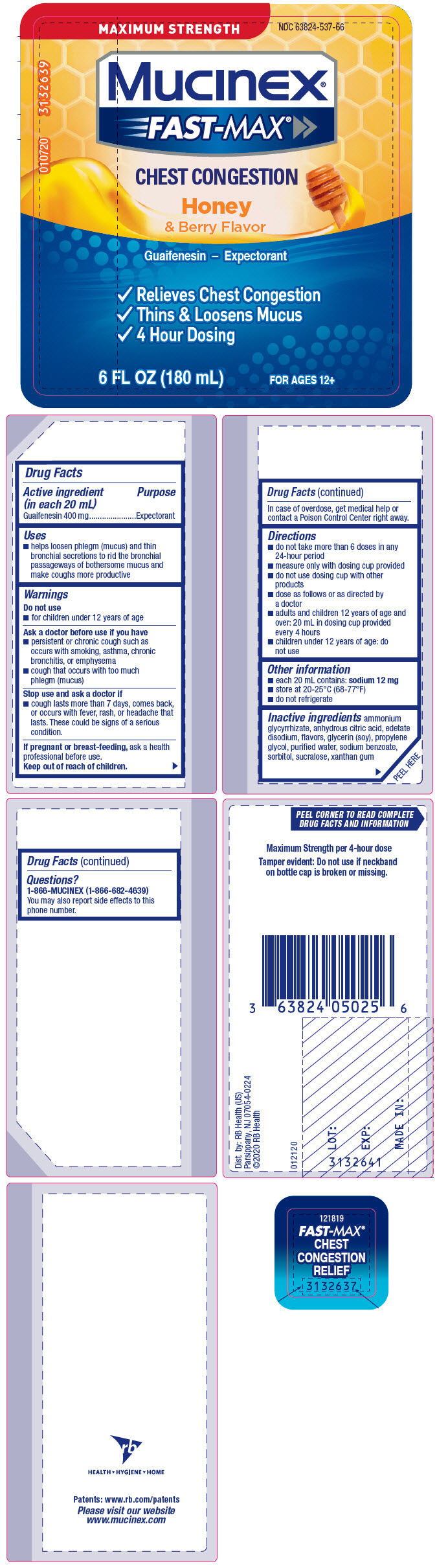 DRUG LABEL: Mucinex Fast-Max Chest Congestion Honey and Berry Flavor
NDC: 63824-537 | Form: SOLUTION
Manufacturer: RB Health (US) LLC
Category: otc | Type: HUMAN OTC DRUG LABEL
Date: 20241227

ACTIVE INGREDIENTS: GUAIFENESIN 400 mg/20 mL
INACTIVE INGREDIENTS: AMMONIUM GLYCYRRHIZATE; ANHYDROUS CITRIC ACID; EDETATE DISODIUM; PROPYLENE GLYCOL; WATER; SODIUM BENZOATE; SORBITOL; SUCRALOSE; XANTHAN GUM

Mucinex® Fast-Max®Chest Congestion Honey & Berry Flavor

Drug Facts

Active ingredient (in each 20 mL)

Guaifenesin 400 mg

Purpose

Expectorant

Uses

- helps loosen phlegm (mucus) and thin bronchial secretions to rid the bronchial passageways of bothersome mucus and make coughs more productive

Warnings

Do not use

- for children under 12 years of age

Ask a doctor before use if you have

- persistent or chronic cough such as occurs with smoking, asthma, chronic bronchitis, or emphysema
- cough that occurs with too much phlegm (mucus)

Stop use and ask a doctor if

- cough lasts more than 7 days, comes back, or occurs with fever, rash, or headache that lasts. These could be signs of a serious condition.

PREGNANCY OR BREAST FEEDING

If pregnant or breast-feeding,ask a health professional before use.

Keep out of reach of children.

In case of overdose, get medical help or contact a Poison Control Center right away.

Directions

- do not take more than 6 doses in any 24-hour period
- measure only with dosing cup provided
- do not use dosing cup with other products
- dose as follows or as directed by a doctor
- adults and children 12 years of age and over: 20 mL in dosing cup provided every 4 hours
- children under 12 years of age: do not use

Other information

- each 20 mL contains: sodium 12 mg
- store at 20-25°C (68-77°F)
- do not refrigerate

Inactive ingredients

ammonium glycyrrhizate, anhydrous citric acid, edetate disodium, flavors, glycerin (soy), propylene glycol, purified water, sodium benzoate, sorbitol, sucralose, xanthan gum

Questions?

1-866-MUCINEX (1-866-682-4639)

You may also report side effects to this phone number.

Dist. by: RB Health (US)
Parsippany, NJ 07054-0224

PRINCIPAL DISPLAY PANEL - 180 mL Bottle Label

MAXIMUM STRENGTH
NDC 63824-537-66

Mucinex®
FAST-MAX®

CHEST CONGESTION

Honey
& Berry Flavor

Guaifenesin – Expectorant

- Relieves Chest Congestion
- Thins & Loosens Mucus
- 4 Hour Dosing

6 FL OZ (180 mL)
FOR AGES 12+

010720
3132639